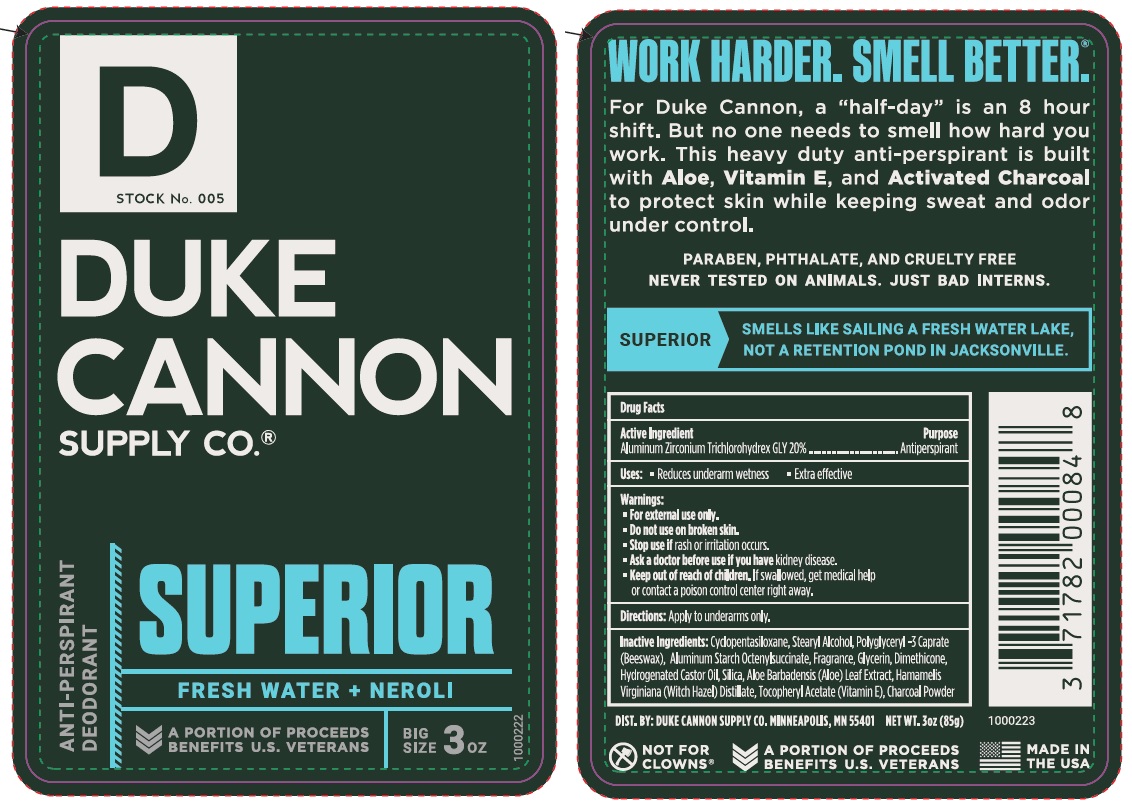 DRUG LABEL: Duke Cannon Superior
NDC: 10889-429 | Form: STICK
Manufacturer: VVF Kansas Services LLC
Category: otc | Type: HUMAN OTC DRUG LABEL
Date: 20221229

ACTIVE INGREDIENTS: ALUMINUM ZIRCONIUM TRICHLOROHYDREX GLY 17 g/85 g
INACTIVE INGREDIENTS: ALUMINUM STARCH OCTENYLSUCCINATE; STEARYL ALCOHOL; HYDROGENATED CASTOR OIL; ACTIVATED CHARCOAL; CYCLOMETHICONE 5; GLYCERIN

Duke Cannon Antiperspirant - Superior

Active Ingredient

Aluminum Zirconium Trichlorohydrex GLY 20%

Purpose

Antiperspirant

Uses

• Reduces underarm wetness

• Extra effective

Warnings:

For external use only.

Do not use on broken skin.

Stop use if rash or irritation occurs.

Ask a doctor before use if you have kidney disease.

Keep out of reach of children.

If swallowed, get medical help or contact a poison control center right away.

Directions:

Apply to underarms only.

Inactive Ingredients

Cyclopentasiloxane, Stearyl Alcohol, Polyglyceryl-3 Caprate (Beeswax),

Aluminum Starch Octenylsuccinate, Fragrance, Glycerin, Dimethicone,

Hydrogenated Castor Oil, Silica, Aloe Barbadensis (Aloe) Leaf Juice,

Hamamelis Virginiana (Witch Hazel) Distillate, Tocopheryl Acetate (Vitamin E),

Charcoal Powder

DIST. BY: DUKE CANNON SUPPLY CO.

MINNEAPOLIS, MN 55401

MADE IN THE USA